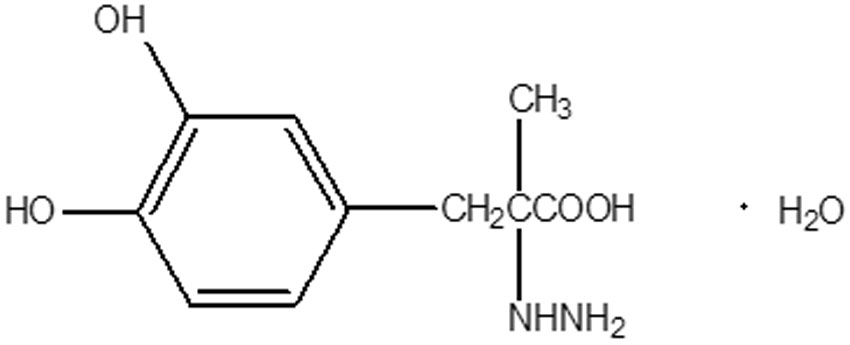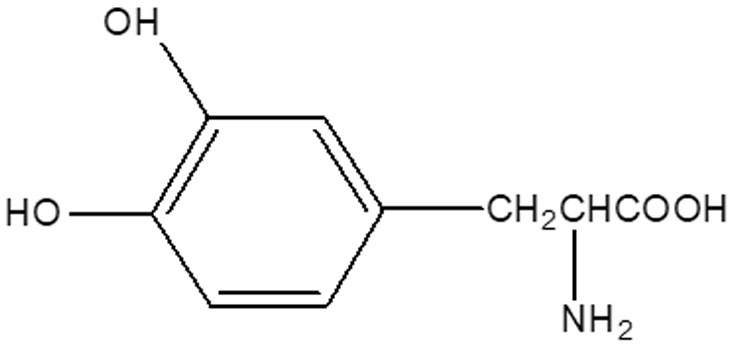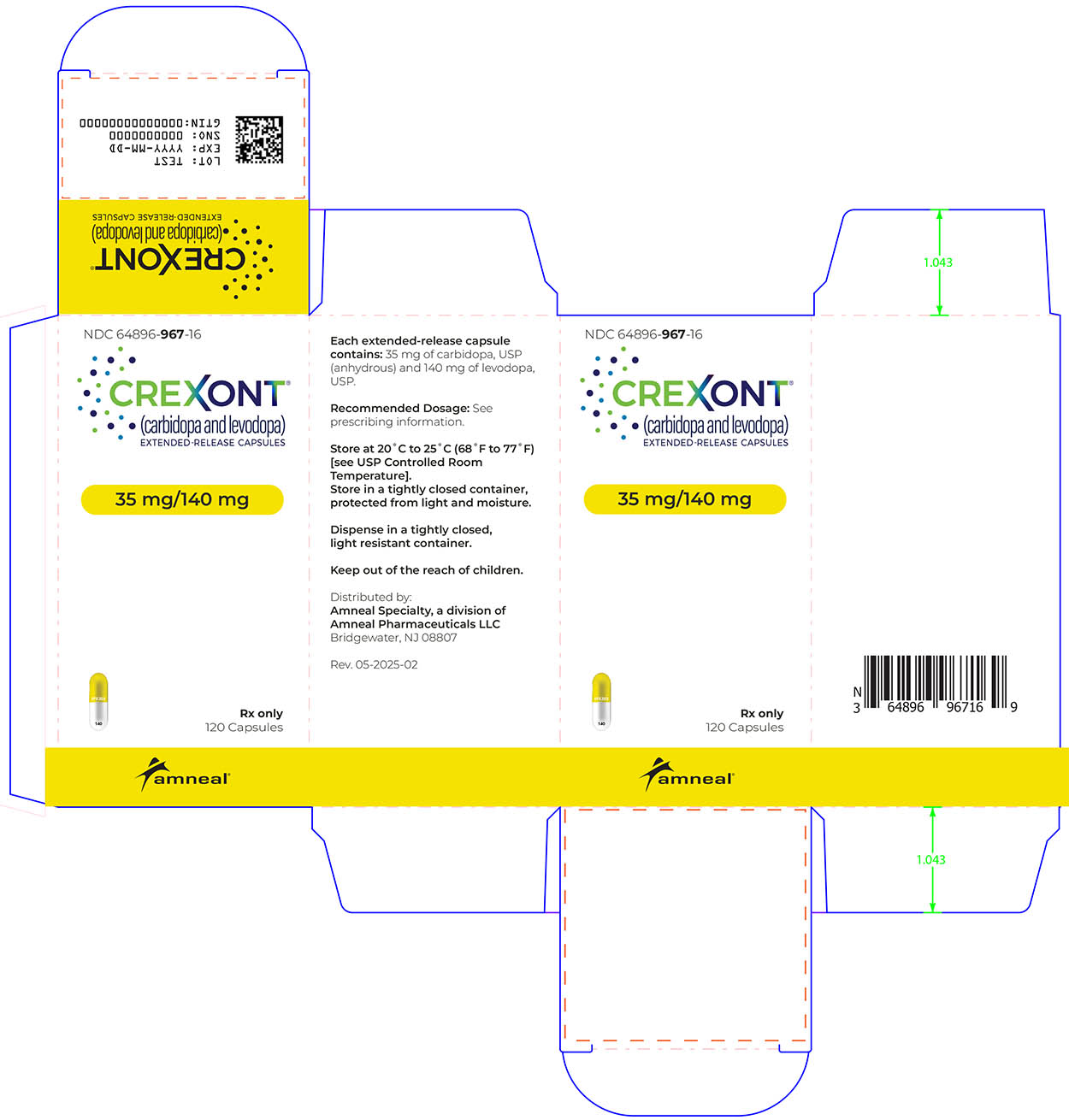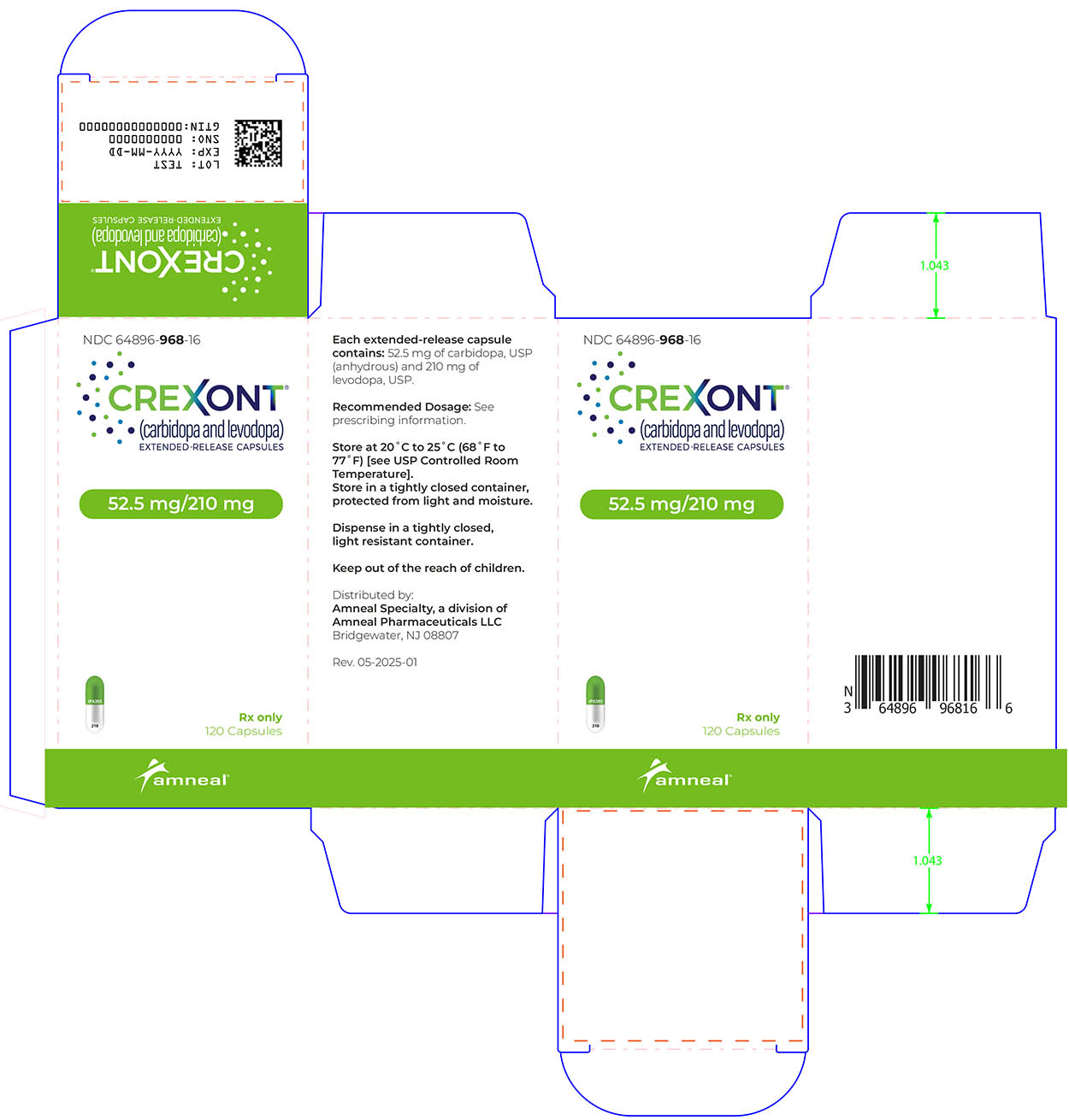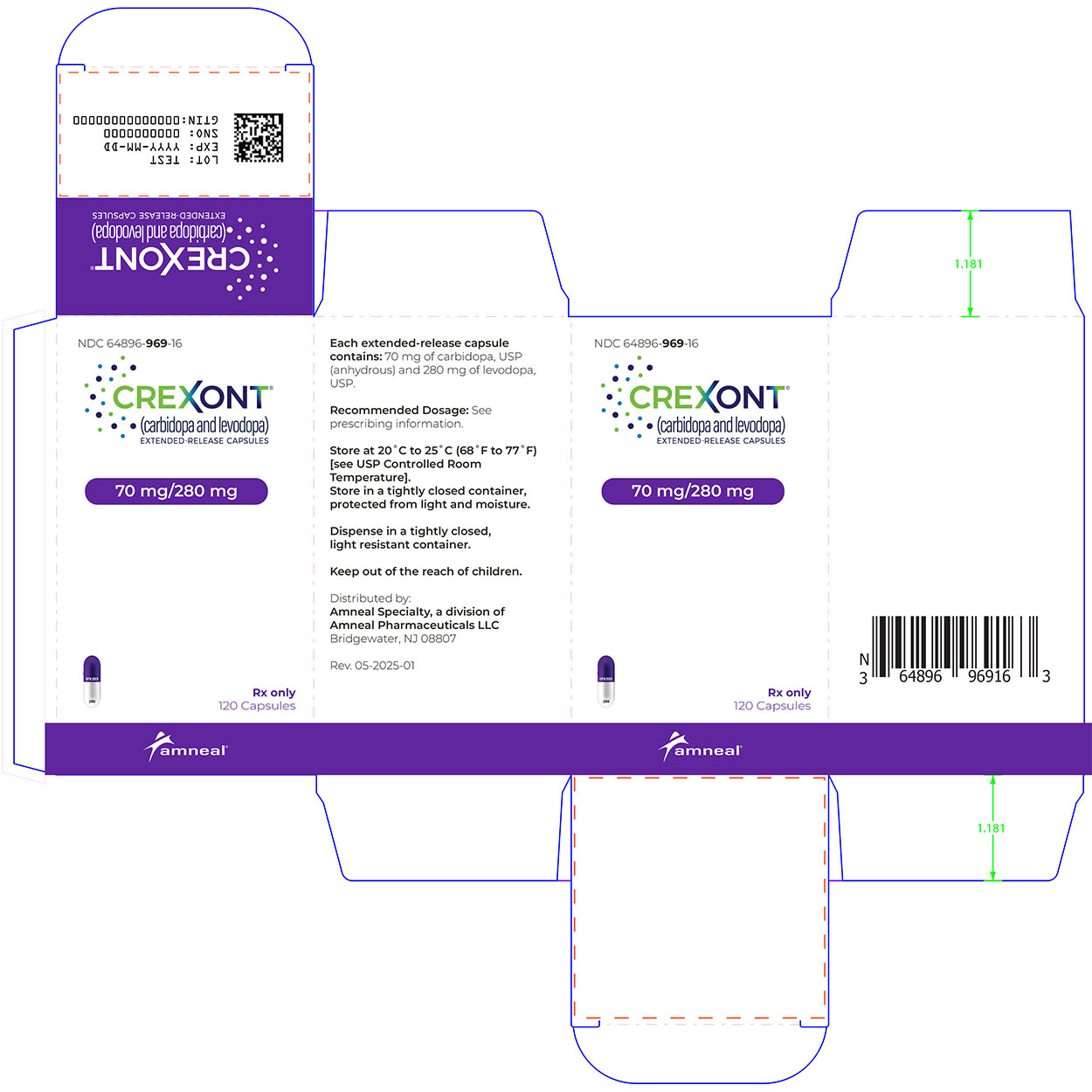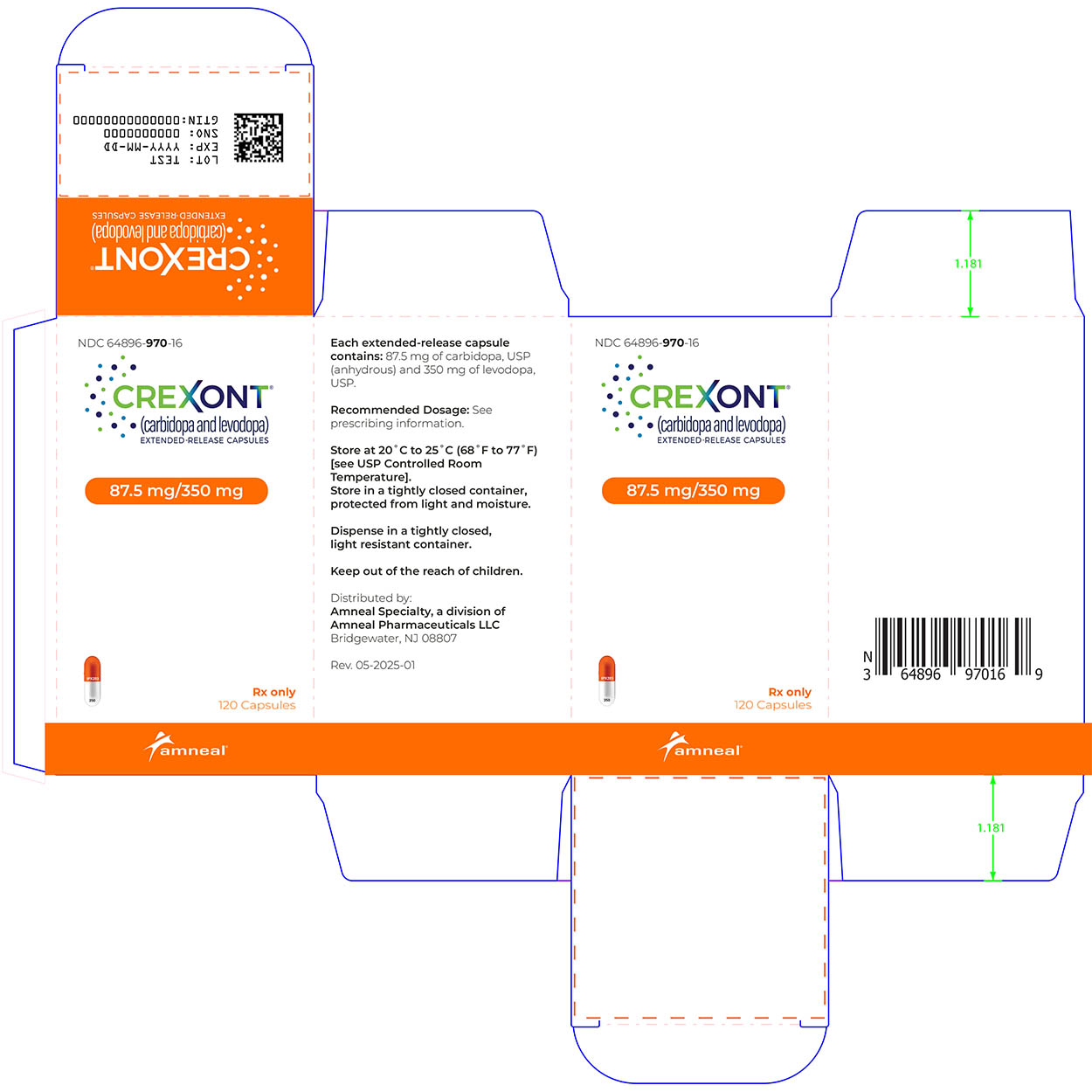 DRUG LABEL: CREXONT
NDC: 64896-967 | Form: CAPSULE, EXTENDED RELEASE
Manufacturer: Amneal Pharmaceuticals LLC
Category: prescription | Type: HUMAN PRESCRIPTION DRUG LABEL
Date: 20250212

ACTIVE INGREDIENTS: CARBIDOPA 35 mg/1 1; LEVODOPA 140 mg/1 1
INACTIVE INGREDIENTS: CELLULOSE ACETATE; COPOVIDONE K25-31; CROSCARMELLOSE SODIUM; DIMETHYLAMINOETHYL METHACRYLATE - BUTYL METHACRYLATE - METHYL METHACRYLATE COPOLYMER; METHACRYLIC ACID - METHYL METHACRYLATE COPOLYMER (1:1); MAGNESIUM STEARATE; MANNITOL; MICROCRYSTALLINE CELLULOSE; POVIDONE; SODIUM LAURYL SULFATE; TALC; TRIETHYL CITRATE; GELATIN; TITANIUM DIOXIDE; D&C YELLOW NO. 10; FERRIC OXIDE RED; AMMONIA; ALCOHOL; FERROSOFERRIC OXIDE; ISOPROPYL ALCOHOL; BUTYL ALCOHOL; PROPYLENE GLYCOL; SHELLAC; SODIUM HYDROXIDE

HIGHLIGHTS OF PRESCRIBING INFORMATION

These highlights do not include all the information needed to use CREXONT® safely and effectively. See full prescribing information for CREXONT.
CREXONT® (carbidopa and levodopa) extended-release capsules, for oral use
Initial U.S. Approval: 1975

1 INDICATIONS AND USAGE

CREXONT is a combination of carbidopa (an aromatic amino acid decarboxylation inhibitor) and levodopa (an aromatic amino acid) indicated for the treatment of Parkinson’s disease, post-encephalitic parkinsonism, and parkinsonism that may follow carbon monoxide intoxication or manganese intoxication in adults. (1)

2 DOSAGE AND ADMINISTRATION

- Levodopa-naïve patients: Starting dose is 35 mg carbidopa / 140 mg levodopa taken orally twice daily for the first 3 days; on the fourth day of treatment, dosage may be increased gradually as needed. (2.1)
- Patients converting from immediate-release carbidopa/levodopa: See Table 1 for instructions; dosages are not substitutable on a 1:1 basis. (2.2)
- The maximum recommended daily dosage of CREXONT is 525 mg carbidopa / 2100 mg levodopa. (2.1, 2.2)
- CREXONT may be taken with or without food; do not chew, divide, or crush. (2.4, 12.3)
- CREXONT should not be taken with alcohol. (2.4, 12.3)

3 DOSAGE FORMS AND STRENGTHS

Extended-Release Capsules: Carbidopa and Levodopa 35 mg / 140 mg, 52.5 mg / 210 mg, 70 mg / 280 mg, 87. 5 mg / 350 mg (3)

4 CONTRAINDICATIONS

- Nonselective MAO inhibitors (4)

5 WARNINGS AND PRECAUTIONS

- May cause falling asleep during activities of daily living. (5.1)
- Avoid sudden discontinuation or rapid dose reduction to reduce the risk of withdrawal-emergent hyperpyrexia and confusion. (5.2)
- Cardiovascular Events: Monitor patients with a history of cardiovascular disease. (5.3)
- Hallucinations/Psychosis may occur. (5.4)
- Impulse Control Disorders: Consider dose reduction or stopping CREXONT if occurs. (5.5)
- May cause or exacerbate dyskinesia: Consider dose reduction. (5.6)

6 ADVERSE REACTIONS

The most common adverse reactions (incidence ≥ 3% and greater than immediate-release CD-LD) are nausea and anxiety. (6.1)

To report SUSPECTED ADVERSE REACTIONS, contact Amneal Pharmaceuticals at 1-877-835-5472 or FDA at 1-800-FDA-1088 or www.fda.gov/medwatch.

7 DRUG INTERACTIONS

Iron salts and dopamine D2 antagonists, including metoclopramide, may reduce the effectiveness of CREXONT. (7.2, 7.3)

8 USE IN SPECIFIC POPULATIONS

Pregnancy: Based on animal data, may cause fetal harm. (8.1)

FULL PRESCRIBING INFORMATION

1 INDICATIONS AND USAGE

CREXONT is indicated for the treatment of Parkinson's disease, post-encephalitic parkinsonism, and parkinsonism that may follow carbon monoxide intoxication or manganese intoxication in adults.

2 DOSAGE AND ADMINISTRATION

2.1 Dosage in Patients Naïve to Levodopa Therapy

The recommended starting dosage of CREXONT in levodopa-naïve patients is 35 mg carbidopa / 140 mg levodopa taken orally twice daily for the first three days. Thereafter, dosage may be increased gradually as needed to a maximum daily dosage of 525 mg carbidopa / 2100 mg levodopa divided up to four times daily.

2.2 Dosage in Patients Converting from Immediate-Release Carbidopa-Levodopa to CREXONT

The dosages of immediate-release carbidopa-levodopa products are not substitutable on a 1:1 basis with the dosages of CREXONT.

To convert patients from immediate-release carbidopa-levodopa to CREXONT, follow these steps:

Step 1: Determine the patient’s total daily dosage of immediate-release levodopa.

Step 2: Determine the patient’s most frequent single dose of immediate-release levodopa. If more than one dose corresponds to the most frequent, use the highest of the doses.

Step 3: Find the values from Step 1 and Step 2 in Table 1 (below) to determine the recommended starting CREXONT dosage of levodopa and dosing frequency.

Step 4: After one to three days, adjust the dose or frequency as needed based on the patient’s clinical response and tolerability. Dosage may be increased gradually as needed to a maximum daily dosage of 525 mg carbidopa / 2100 mg levodopa divided up to four times daily.

Table 1: Conversion from Immediate-Release Carbidopa-Levodopa to CREXONT

Total Daily; Immediate-Release; Levodopa Dosage | Most Frequent Immediate-Release Levodopa Single Dose | Recommended Starting CREXONT Dosage of Levodopa
Less than 500 mg daily | 100 mg | 280 mg twice daily
Less than 500 mg daily | 150 mg | 420 mg twice daily
Less than 500 mg daily | 200 mg | 560 mg twice daily
Equal to or greater than 500 mg daily | 100 mg | 280 mg three times daily
Equal to or greater than 500 mg daily | 150 mg | 420 mg three times daily
Equal to or greater than 500 mg daily | 200 mg | 560 mg three times daily
Equal to or greater than 500 mg daily | Greater than 200 mg | 700 mg three times daily

For patients currently treated with carbidopa and levodopa plus a catechol-O-methyl transferase (COMT) inhibitor (e.g., entacapone or opicapone), the initial total daily dose of levodopa in CREXONT may need to be increased if the COMT inhibitor is discontinued.

Use of CREXONT in combination with other levodopa products has not been studied.

2.3 Dosage for Patients Converting from Extended-Release Carbidopa-Levodopa (Rytary) to CREXONT

For patients converting from RYTARY (extended-release carbidopa-levodopa), initiate CREXONT on an approximately 1:1 mg basis using the levodopa component for conversion.

2.4 Administration Information

Swallow CREXONT whole with or without food. CREXONT should not be taken with alcohol. A high-fat, high-calorie meal may delay the absorption of levodopa to reach the peak plasma concentration by about 2 hours [see Clinical Pharmacology (12.3)].

Do not chew, divide, or crush CREXONT capsules.

2.5 Discontinuation of CREXONT

Avoid sudden discontinuation or rapid dose reduction of CREXONT. The daily dose of CREXONT should be tapered at the time of treatment discontinuation [see Warnings and Precautions (5.2)].

3 DOSAGE FORMS AND STRENGTHS

CREXONT extended-release capsules contain white to off-white granules and pellets and are available in the following strengths:

- 35 mg carbidopa and 140 mg levodopa: Capsules with white opaque body and yellow opaque cap. Body imprinted with “140” in black ink and cap imprinted with “IPX203” in white ink.
- 52.5 mg carbidopa and 210 mg levodopa: Capsules with white opaque body and green opaque cap. Body imprinted with “210” in black ink and cap imprinted with “IPX203” in white ink.
- 70 mg carbidopa and 280 mg levodopa: Capsules with white opaque body and purple opaque cap. Body imprinted with “280” in black ink and cap imprinted with “IPX203” in white ink.
- 87.5 mg carbidopa and 350 mg levodopa: Capsules with white opaque body and medium orange opaque cap. Body imprinted with “350” in black ink and cap imprinted with “IPX203” in white ink.

4 CONTRAINDICATIONS

CREXONT is contraindicated in patients currently taking a nonselective monoamine oxidase (MAO) inhibitor or have recently (within 2 weeks) taken a nonselective MAO inhibitor. Hypertension can occur if these drugs are used concurrently [see Drug Interactions (7.1)].

5 WARNINGS AND PRECAUTIONS

5.1 Falling Asleep During Activities of Daily Living and Somnolence

Patients treated with levodopa, a component of CREXONT, have reported falling asleep while engaged in activities of daily living, including the operation of motor vehicles, which sometimes resulted in accidents. Although many of these patients reported somnolence while on levodopa, some perceived that they had no warning signs, such as excessive drowsiness, and believed that they were alert immediately prior to the event (sleep attack). Some of these events have been reported more than 1 year after initiation of treatment.

Falling asleep while engaged in activities of daily living usually occurs in patients experiencing preexisting somnolence, although patients may not give such a history. For this reason, prescribers should reassess for drowsiness or sleepiness in CREXONT-treated patients, especially since some of the events occur well after the start of treatment. Prescribers should also be aware that patients may not acknowledge drowsiness or sleepiness until directly questioned about drowsiness or sleepiness during specific activities.

Before initiating treatment with CREXONT, advise patients of the potential to develop drowsiness and specifically ask about factors that may increase the risk for somnolence with CREXONT, such as concomitant sedating medications or the presence of a sleep disorder. Consider discontinuing CREXONT in patients who report significant daytime sleepiness or episodes of falling asleep during activities that require active participation (e.g., conversations, eating, etc.).

If a decision is made to continue CREXONT, patients should be advised not to drive and to avoid other potentially dangerous activities that might result in harm if the patients become somnolent. There is insufficient information to establish that dose reduction will eliminate episodes of falling asleep while engaged in activities of daily living.

5.2 Withdrawal-Emergent Hyperpyrexia and Confusion

A symptom complex that resembles neuroleptic malignant syndrome (characterized by elevated temperature, muscular rigidity, altered consciousness, and autonomic instability), with no other obvious etiology, has been reported in association with rapid dose reduction, withdrawal of, or changes in dopaminergic therapy. Avoid sudden discontinuation or rapid dose reduction in patients taking CREXONT. If the decision is made to discontinue CREXONT, the dose should be tapered to reduce the risk of hyperpyrexia and confusion [see Dosage and Administration (2.5)].

5.3 Cardiovascular Ischemic Events

Cardiovascular ischemic events have occurred in patients taking CREXONT. In Study 1 [see Clinical Studies (14)], 4/589 (0.7%) of CREXONT-treated patients experienced cardiovascular ischemic adverse reactions compared to 2/630 (0.3%) of oral immediate-release carbidopa-levodopa-treated patients. These patients all had a previous history of ischemic heart disease or risk factors for ischemic heart disease.

In patients with a history of myocardial infarction who have residual atrial, nodal, or ventricular arrhythmias, cardiac function should be monitored in an intensive cardiac care facility during the period of initial dosage adjustment.

5.4 Hallucinations/Psychosis

There is an increased risk for hallucinations in patients taking CREXONT. In Study 1, 17/589 (3%) of CREXONT-treated patients reported hallucinations compared to 2/630 (0.3%) of oral immediate-release carbidopa-levodopa-treated patients.

Hallucinations present shortly after the initiation of therapy and may be responsive to dose reduction in levodopa. Hallucinations may be accompanied by confusion, insomnia, and excessive dreaming. Abnormal thinking and behavior may present with one or more symptoms, including paranoid ideation, delusions, hallucinations, confusion, psychotic-like behavior, disorientation, aggressive behavior, agitation, and delirium.

Because of the risk of exacerbating psychosis, patients with a major psychotic disorder should not be treated with CREXONT. In addition, medications that antagonize the effects of dopamine used to treat psychosis may exacerbate the symptoms of Parkinson’s disease and may decrease the effectiveness of CREXONT [see Drug Interactions (7.2)].

5.5 Impulse Control/Compulsive Behaviors

Case reports suggest that patients can experience intense urges to gamble, increased sexual urges, intense urges to spend money, binge eating, and/or other intense urges, and the inability to control these urges while taking one or more of the medications, including CREXONT, that increase central dopaminergic tone and that are generally used for the treatment of Parkinson’s disease. In some cases, although not all, these urges were reported to have stopped when the dose was reduced or the medication was discontinued.

Because patients may not recognize these behaviors as abnormal, it is important for prescribers to specifically ask patients or their caregivers about the development of new or increased gambling urges, sexual urges, uncontrolled spending, or other urges while being treated with CREXONT. Consider a dose reduction or stopping the medication if a patient develops such urges while taking CREXONT.

5.6 Dyskinesia

CREXONT can cause dyskinesias that may require a dosage reduction of CREXONT or other medications used for the treatment of Parkinson’s disease.

5.7 Peptic Ulcer Disease

Treatment with CREXONT may increase the possibility of upper gastrointestinal hemorrhage in patients with a history of peptic ulcer.

5.8 Glaucoma

CREXONT may cause increased intraocular pressure in patients with glaucoma. Monitor intraocular pressure in patients with glaucoma after starting CREXONT.

6 ADVERSE REACTIONS

The following serious adverse reactions are discussed below and elsewhere in the labeling:

- Falling Asleep During Activities of Daily Living and Somnolence [see Warnings and Precautions (5.1)]
- Withdrawal-Emergent Hyperpyrexia and Confusion [see Warnings and Precautions (5.2)]
- Cardiovascular Ischemic Events [see Warnings and Precautions (5.3)]
- Hallucinations/Psychosis [see Warnings and Precautions (5.4)]
- Impulse Control/Compulsive Behaviors [see Warnings and Precautions (5.5)]
- Dyskinesia [see Warnings and Precautions (5.6)]
- Peptic Ulcer Disease [see Warnings and Precautions (5.7)]
- Glaucoma [see Warnings and Precautions (5.8)]

6.1 Clinical Trials Experience

Because clinical trials are conducted under widely varying conditions, adverse reaction rates observed in the clinical trials of a drug cannot be directly compared to rates in the clinical trials of another drug and may not reflect the rates observed in clinical practice.

The safety population consisted of 589 patients with Parkinson’s disease who received CREXONT for up to 76 weeks and had an average duration of exposure of 35 weeks. Study 1 in patients with Parkinson’s Disease consisted of a dose adjustment period of immediate-release carbidopa-levodopa treatment prior to a 4-week dose conversion period to CREXONT, which was then followed by a 13-week, double-blind, randomized period comparing CREXONT to immediate-release carbidopa-levodopa [see Clinical Studies (14)].

In Study 1, the most common adverse reactions (in at least 3% of patients treated with CREXONT and more frequently than with immediate-release carbidopa-levodopa) that occurred during the double-blind maintenance period were nausea and anxiety.

Table 2 lists adverse reactions occurring in at least 2% of CREXONT-treated patients while converting from immediate-release carbidopa-levodopa and at a higher rate than immediate-release carbidopa-levodopa in the double-blind maintenance period.

Table 2. Adverse Reactions that Occurred in at Least 2% of Patients with Parkinson’s Disease who Received CREXONT and at a Higher Rate than Patients who Received Immediate-Release Carbidopa-Levodopa (Study 1)

Adverse Reaction | Dose Conversion Period | Double-Blind Period
Adverse Reaction | CREXONT | CREXONT | Immediate-Release Carbidopa-Levodopa
Adverse Reaction | (N=589); % | (N=256); % | (N= 250); %
Nausea | 5 | 4 | 1
Anxiety | 2 | 3 | 0
Dizziness | 3 | 2 | 1
Dyskinesia | 7 | 2 | 0.4
Constipation | 2 | 2 | 0.4
Headache | 2 | 1 | 0
Vomiting | 2 | 1 | 0
Insomnia | 2 | 1 | 0.4

Adverse Reactions Leading to Discontinuation

In Study 1, 6% of patients discontinued treatment because of adverse reactions during conversion to CREXONT. During the double-blind treatment period of Study 1, 5% of patients taking CREXONT and 1% of patients taking immediate-release carbidopa-levodopa discontinued treatment because of adverse events.

The common adverse reactions leading to drug discontinuation during dose conversion were dyskinesia, dizziness, and nausea.

7 DRUG INTERACTIONS

7.1 Monoamine Oxidase (MAO) Inhibitors

Nonselective MAO Inhibitors

The use of nonselective MAO inhibitors (e.g., phenelzine and tranylcypromine) with CREXONT is contraindicated [see Contraindications (4)]. Discontinue use of any nonselective MAO inhibitors at least two weeks prior to initiating CREXONT.

Selective MAO Inhibitors

The use of selective MAO-B inhibitors (e.g., rasagiline and selegiline) with CREXONT may be associated with orthostatic hypotension. Monitor patients who are taking these drugs concurrently.

7.2 Dopamine D2 Receptor Antagonists and Isoniazid

Dopamine D2 receptor antagonists (e.g., phenothiazines, butyrophenones, risperidone, metoclopramide) and isoniazid may reduce the effectiveness of levodopa. Monitor patients for worsening Parkinson’s symptoms.

7.3 Iron Salts

Iron salts or multivitamins containing iron salts can form chelates with levodopa and carbidopa and can cause a reduction in the bioavailability of CREXONT. If iron salts or multivitamins containing iron salts are co-administered with CREXONT, monitor patients for worsening Parkinson’s symptoms.

8 USE IN SPECIFIC POPULATIONS

8.1 Pregnancy

Risk Summary

There are no adequate data on the developmental risk associated with the use of CREXONT (carbidopa and levodopa) in pregnant women. In animal studies, carbidopa-levodopa has been shown to be developmentally toxic (including teratogenic effects) at clinically relevant doses (see Data).

The estimated background risk of major birth defects and miscarriage in the indicated population is unknown. In the U.S. general population, the estimated background risk of major birth defects and miscarriage in clinically recognized pregnancies is 2% to 4% and 15% to 20%, respectively.

Data

Animal Data

When administered to pregnant rabbits throughout organogenesis, carbidopa-levodopa caused both visceral and skeletal malformation in fetuses at all doses and ratios of carbidopa-levodopa tested. No teratogenic effects were observed when carbidopa-levodopa was administered to pregnant mice throughout organogenesis.

There was a decrease in the number of live pups delivered by rats receiving carbidopa-levodopa during organogenesis.

8.2 Lactation

Risk Summary

CREXONT is a combination of carbidopa and levodopa.

Carbidopa

There are no adequate data on the presence of carbidopa in human milk, the effects on the breastfed infant, or the effects on milk production. Carbidopa is excreted in rat milk.

Levodopa

Levodopa has been detected in human milk after administration of carbidopa-levodopa. Levodopa decreases secretion of prolactin in humans, which may inhibit lactation. There are no adequate data on the effects of levodopa on the breastfed infant.

The developmental and health benefits of breastfeeding should be considered along with the mother’s clinical need for CREXONT and any potential adverse effects on the breastfed infant from CREXONT or from the underlying maternal condition.

8.4 Pediatric Use

Safety and effectiveness in pediatric patients have not been established.

8.5 Geriatric Use

There were 282 (45%) patients 65 to less than 74 years of age and 112 (18%) patients 75 years of age and older treated with CREXONT in an active-controlled study for Parkinson’s disease (Study 1) [see Clinical Studies (14)]. There were no differences in safety outcomes between patients less than 65 years of age, 65 to less than 75 years of age, or 75 years and older.

10 OVERDOSAGE

Based on the limited available information, the acute symptoms of levodopa/carbidopa overdosage can be expected to arise from dopaminergic overstimulation. Doses of a few grams may result in CNS disturbances, with an increasing likelihood of cardiovascular disturbance (e.g., hypotension, tachycardia) and more severe psychiatric problems at higher doses. An isolated report of rhabdomyolysis and another of transient renal insufficiency suggest that levodopa overdosage may give rise to systemic complications, secondary to dopaminergic overstimulation.

In the event of CREXONT overdosage, monitor patients and provide supportive care. Patients should receive electrocardiographic monitoring for the development of arrhythmias; if needed, appropriate antiarrhythmic therapy should be given. The possibility that the patient may have taken other drugs, increasing the risk of drug interactions (especially catechol-structured drugs) should be taken into consideration.

11 DESCRIPTION

CREXONT is a combination of carbidopa, an inhibitor of aromatic amino acid decarboxylation, and levodopa, an aromatic amino acid, in extended-release capsules for oral use.

CREXONT contains immediate-release granules consisting of carbidopa and levodopa and extended-release pellets consisting of levodopa.

Carbidopa is a white to off-white powder, crystalline compound, slightly soluble in water, with a molecular weight of 244.24. It is designated chemically as (–)-L-α-hydrazino-α-methyl-β-(3,4-dihydroxy-benzene) propanoic acid monohydrate. Its molecular formula is C10H14N2O4•H2O and its structural formula is:

Capsule content is expressed in terms of anhydrous carbidopa, which has a molecular weight of 226.3.

Levodopa is a white, crystalline compound, slightly soluble in water, with a molecular weight of 197.2. It is designated chemically as (–)-L-α-amino-β-(3,4-dihydroxy-benzene) propanoic acid. Its molecular formula is C9H11NO4 and its structural formula is:

Each CREXONT extended-release capsule contains 35 mg carbidopa and 140 mg levodopa, 52.5 mg carbidopa and 210 mg levodopa, 70 mg carbidopa and 280 mg levodopa, or 87.5 mg carbidopa and 350 mg levodopa. The inactive ingredients are amino methacrylate copolymer, cellulose acetate, copovidone, croscarmellose sodium, magnesium stearate, mannitol, methacrylic acid and methyl methacrylate copolymer, microcrystalline cellulose, povidone, sodium lauryl sulfate, talc, and triethyl citrate.

- The 35mg/140 mg capsule shell contains D&C yellow #10, gelatin, Red Iron Oxide, and titanium dioxide.
- The 52.5 mg/210 mg capsule shell contains FD&C Blue #1, gelatin, titanium dioxide, and yellow iron oxide.
- The 70 mg/280 mg capsule shell contains FD&C Blue #1, FD&C Red #3, gelatin, and titanium dioxide.
- The 87.5 mg/350 mg capsule shell contains gelatin, Red Iron Oxide, titanium dioxide, and yellow iron oxide.
- The black imprinting ink contains ammonium hydroxide, ethanol, ferrosoferric oxide/black iron oxide, isopropyl alcohol, n-butyl alcohol, propylene glycol, and shellac glaze.
- The white imprinting ink contains ethanol, isopropyl alcohol, n-butyl alcohol, povidone, propylene glycol, shellac glaze, sodium hydroxide, and titanium dioxide.

12 CLINICAL PHARMACOLOGY

12.1 Mechanism of Action

Carbidopa

When levodopa is administered orally, it is rapidly decarboxylated to dopamine in extracerebral tissues so that only a small portion of a given dose is transported unchanged to the central nervous system. Carbidopa inhibits the decarboxylation of peripheral levodopa, making more levodopa available for delivery to the brain.

Levodopa

Levodopa is the metabolic precursor of dopamine, does cross the blood-brain barrier, and presumably is converted to dopamine in the brain. This is thought to be the mechanism whereby levodopa treats symptoms of Parkinson's disease.

12.2 Pharmacodynamics

Because its decarboxylase inhibiting activity is limited to extracerebral tissues, administration of carbidopa with levodopa makes more levodopa available to the brain. The addition of carbidopa to levodopa reduces the peripheral effects (nausea, vomiting) due to decarboxylation of levodopa; however, carbidopa does not decrease the adverse reactions due to the central effects of levodopa.

Patients treated with levodopa therapy for Parkinson's disease may develop motor fluctuations characterized by end-of-dose failure, peak dose dyskinesia, ‘on-off’ phenomenon, and akinesia.

Cardiac Electrophysiology

At exposures corresponding to the maximum recommended dose of carbidopa in CREXONT, clinically significant QTc interval prolongation was not observed.

12.3 Pharmacokinetics

The pharmacokinetics of CREXONT were evaluated following single doses in healthy subjects and following single and multiple doses in patients with Parkinson’s disease.

CREXONT shows dose proportional pharmacokinetics for both carbidopa and levodopa over the carbidopa/levodopa dosage strength range of 35 mg/140 mg to 87.5 mg/350 mg.

Absorption

Carbidopa

Following oral dosing of CREXONT, the maximum concentration occurred at approximately 2.5 hours. The bioavailability of carbidopa from CREXONT relative to immediate-release carbidopa-levodopa tablets was approximately 103% to 123%.

Levodopa

The bioavailability of levodopa from CREXONT was approximately 88% to 99% relative to immediate-release carbidopa-levodopa.

For comparable doses, CREXONT results in a levodopa peak concentration (Cmax) that is 38% that of immediate-release carbidopa-levodopa. Following an initial peak at about one hour, plasma concentrations were maintained for about 6 to 7 hours before declining.

In patients with Parkinson’s disease, multiple-dose pharmacokinetics was comparable to single-dose pharmacokinetics, i.e., there was minimal accumulation of levodopa. Variation in levodopa peak to trough plasma concentrations at steady-state defined as (Cmax-Cmin)/Cavg was approximately 1.7 for CREXONT compared to approximately 2.7 for immediate-release carbidopa-levodopa.

Effect of Food

Carbidopa

In healthy adults, oral administration of CREXONT after a high-fat, high-calorie meal decreased both Cmax and AUC by approximately 64% for carbidopa compared to administration in the fasted state. The peak plasma concentrations of carbidopa were observed approximately one hour later when CREXONT is taken with a high-fat high-calorie meal.

Levodopa

In healthy adults, oral administration of CREXONT after a high-fat, high-calorie meal increased Cmax approximately 19% and AUC0-∞ approximately 18% for levodopa compared to administration in the fasted state [see Dosage and Administration (2.4)]. The peak plasma concentrations of levodopa were observed approximately two hours later when CREXONT is taken with a high-fat, high-calorie meal. In addition, absorption of levodopa may be decreased by a high protein meal.

Distribution

Approximately 36% of carbidopa binds to plasma proteins. Approximately 10% to 30% of levodopa binds to plasma proteins.

Metabolism and Elimination

Carbidopa

The terminal phase elimination half-life of carbidopa is approximately 2 hours.

Carbidopa is metabolized to two main metabolites: α-methyl-3-methoxy-4-hydroxyphenylpropionic acid and α-methyl-3,4-dihydroxy-phenylpropionic acid. These two metabolites are primarily eliminated in the urine unchanged or as a glucuronide. Unchanged carbidopa accounts for 30% of the total urinary excretion.

Peripheral dopa-decarboxylase may be saturated by carbidopa in immediate release carbidopa-levodopa products at 70 mg per day to 100 mg per day, which produces similar exposure to 62.5 mg to 89.3 mg per day of carbidopa provided by CREXONT.

Levodopa

The terminal phase elimination half-life of levodopa, the active moiety of antiparkinsonian activity, is approximately 2 hours in the presence of carbidopa.

Levodopa is extensively metabolized to various metabolites. The two major metabolic pathways are decarboxylation by dopa decarboxylase (DDC) and O-methylation by catechol-O-methyltransferase (COMT).

Specific Populations

Geriatric Patients

In pharmacokinetic studies following a single dose of CREXONT, the peak concentrations of carbidopa and levodopa are generally similar between younger (45 to 60 years) and older (60 to 75 years) subjects.

Drug Interaction Studies

In Vitro Studies

Effect of Ethanol

Ethanol-induced dose dumping of CREXONT was observed in the presence of 40% ethanol (80 proof) solution in a dissolution study [see Dosage and Administration (2.4)]; however, dose dumping was not observed in the presence of lower ethanol concentrations. The clinical significance of this dose dumping was not fully characterized in humans.

13 NONCLINICAL TOXICOLOGY

13.1 Carcinogenesis, Mutagenesis, Impairment of Fertility

Carcinogenesis

In rats, oral administration of carbidopa-levodopa for two years resulted in no evidence of carcinogenicity.

Mutagenesis

Carbidopa was mutagenic in the in vitro Ames test and in the in vitro mouse lymphoma tk assay but was negative in the in vivo mouse micronucleus assay.

Impairment of Fertility

In reproduction studies, no effects on fertility were observed in rats receiving carbidopa-levodopa.

14 CLINICAL STUDIES

The effectiveness of CREXONT for the treatment of Parkinson’s disease was established in an active-controlled, multicenter, 20-week clinical trial (Study 1; NCT03670953). Study 1 consisted of a 3-week dose adjustment period of immediate-release carbidopa-levodopa treatment prior to a 4-week conversion period to CREXONT, which was followed by a 13-week, double-blind, double-dummy, randomized, parallel group period comparing CREXONT to immediate-release carbidopa-levodopa. Study 1 enrolled 630 (506 randomized) patients (Hoehn & Yahr Stages I-IV) who had been maintained on a stable regimen of at least 400 mg per day of levodopa prior to entry into the trial and who experienced a minimum of 2.5 hours of “Off” time per day while awake. Patients had a mean age of 67 years and a mean disease duration of 9 years. 96% of the patients were white, 2% were Asian, 1% Black and 63% of the patients were male. At baseline, approximately 73% of patients in the CREXONT group and 63% of patients in the oral IR carbidopa-levodopa group were taking at least 1 or more classes of PD medications other than carbidopa-levodopa. Seventy-four percent of patients were continued on concomitant dopamine agonists (52%), selective monoamine oxidase B (MAO-B) inhibitors (33%), amantadine (19%), and anticholinergics (4%) provided the doses were stable for at least 4 weeks prior to screening. Patients were randomized to receive either immediate-release carbidopa-levodopa or CREXONT at the dose determined during the adjustment or conversion phases. Patients were not allowed to receive supplemental carbidopa-levodopa products or additional carbidopa, any catechol-O-methyl transferase (COMT) inhibitor products, non-selective monoamine oxidase (MAO) inhibitors, selective MAO-A inhibitors, apomorphine, or antidopaminergic agents (including antiemetics) during the trial.

In Study 1, 75% of patients required 2 or fewer titration steps to reach a stable total daily dose of CREXONT.

The mean daily dosage of the levodopa component of CREXONT was 1487 mg.

The primary efficacy measure in Study 1 was the mean change from baseline in “On” time without troublesome dyskinesia in hours per day at the end of the study (Week 20 or at early termination), as assessed by the patient’s Parkinson’s disease diary. “On” time without troublesome dyskinesia was defined as the sum of “On” time without dyskinesia and “On” time with non-troublesome dyskinesia. Patients reported an improvement in “On” time without troublesome dyskinesia with CREXONT compared to immediate-release carbidopa-levodopa which was statistically significant (p=0.019) (Table 3). CREXONT-treated patients also reported less “Off” time compared to immediate-release carbidopa-levodopa, which was statistically significant (p=0.025) (Table 3).

Table 3. Efficacy Results in Patients with Parkinson’s Disease:

 | Week 0; Enrollment | Week 7; Baseline; (Randomization) | Week 20; End of Study; (or Early Termination) | p-value
Mean “On” time without troublesome dyskinesia (hours)
CREXONT | 9.46 | 11.67 | 11.35 | 0.019*
Immediate-release carbidopa-levodopa | 9.61 | 11.72 | 10.77 | 0.019*
Mean “Off” time (hours)
CREXONT | 6.15 | 3.95 | 4.18 | 0.025*
Immediate-release carbidopa-levodopa | 6.05 | 4.02 | 4.75 | 0.025*

* p-value based on change from Week 7 (Baseline) to Week 20 (End of Study or Early Termination)

16 HOW SUPPLIED/STORAGE AND HANDLING

16.1 How Supplied

CREXONT capsules contain white to off-white granules and pellets and are available in bottles of 120 capsules as follows:

Capsule Strength | Description | NDC Number
35 mg Carbidopa and 140 mg Levodopa | Capsules with white opaque body and yellow opaque cap. Body imprinted with “140” in black ink and cap imprinted with “IPX203” in white ink. | 64896-967-16
52.5 mg Carbidopa and 210 mg Levodopa | Capsules with white opaque body and green opaque cap. Body imprinted with “210” in black ink and cap imprinted with “IPX203” in white ink. | 64896-968-16
70 mg Carbidopa and 280 mg Levodopa | Capsules with white opaque body and purple opaque cap. Body imprinted with “280” in black ink and cap imprinted with “IPX203” in white ink. | 64896-969-16
87.5 mg Carbidopa and 350 mg Levodopa | Capsules with white opaque body and medium orange opaque cap. Body imprinted with “350” in black ink and cap imprinted with “IPX203” in white ink. | 64896-970-16

16.2 Storage and Handling

Store at 20°C to 25°C (68°F to 77°F); excursions permitted between 15°C to 30°C (59°F to 86°F) [see USP Controlled Room Temperature]. Store in a tightly closed container, protected from light and moisture.

Dispense in a tightly closed, light-resistant container.

17 PATIENT COUNSELING INFORMATION

Dosing Instructions

- Advise patients not to take other carbidopa-levodopa preparations with CREXONT without consulting their healthcare provider [see Dosage and Administration (2.1)].

- Advise patients to swallow CREXONT whole, without chewing, dividing, or crushing [see Dosage and Administration (2.4)].

- CREXONT should not be taken with alcohol [see Dosage and Administration (2.4) and Clinical Pharmacology (12.3)].

- Inform patients that a high fat, high calorie meal may delay the absorption of levodopa and the onset of action by 2 to 5 hours. For this reason, consideration should be given to taking the first dose of the day about 1 to 2 hours before eating. The patient should also be advised that a change in diet to foods that are high in protein may delay the absorption of levodopa and may reduce the amount taken up in the circulation [see Dosage and Administration (2.4) and Clinical Pharmacology (12.3)].

- Advise patients to call their healthcare provider before stopping CREXONT. Discontinue CREXONT slowly. Tell patients to call their healthcare provider if they develop withdrawal symptoms such as fever, confusion, or severe muscle stiffness [see Dosage and Administration (2.5) and Warnings and Precautions (5.2)].

Falling Asleep During Activities of Daily Living and Somnolence

Advise patients that certain side effects such as sleepiness and dizziness that have been reported with CREXONT may affect some patients’ ability to drive and operate machinery safely [see Warnings and Precautions (5.1) and Adverse Reactions (6.1)].

Suicidal Ideation and Suicidal Behavior

Instruct patients, family members and caregivers to notify their healthcare provider if suicidal ideation and/or suicidal behavior are experienced by patients using CREXONT [see Warnings and Precautions (5.2)].

Hallucinations and Psychosis

Inform patients that hallucinations can occur with levodopa products [see Warnings and Precautions (5.4)].

Impulse Control Disorder

Inform patients of the potential for experiencing intense urges to gamble, increased sexual urges, and other intense urges and the inability to control these urges while taking one or more of the medications that increase central dopaminergic tone, that are generally used for the treatment of Parkinson’s disease [see Warnings and Precautions (5.5)].

Dyskinesia

Instruct patients to notify their healthcare provider if abnormal involuntary movements appear or get worse during treatment with CREXONT [see Warnings and Precautions (5.6)].

Hypotension and Syncope

Advise patients that they may develop orthostatic hypotension with or without symptoms such as dizziness, nausea, syncope, and sweating [see Adverse Reactions (6.1)]. Advise patients to rise slowly after sitting or lying down, especially if they have been doing so for a prolonged period.

Advise patients of the possible additive sedative effects when taking CNS depressants in combination with CREXONT.

Pregnancy and Breastfeeding

Advise patients to notify their healthcare provider if they become pregnant or intend to become pregnant during carbidopa and levodopa extended-release capsule therapy [see Use in Specific Populations (8.1)].

Instruct patients to notify their physicians if they intend to breast-feed or are breast-feeding an infant [see Use in Specific Populations (8.2)].

Distributed by:

Amneal Specialty, a division of Amneal Pharmaceuticals LLC

Bridgewater, NJ 08807

Rev. 02-2025-01